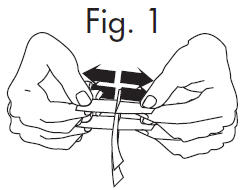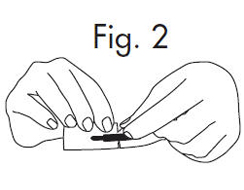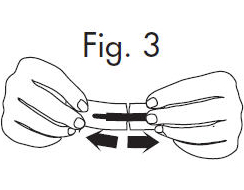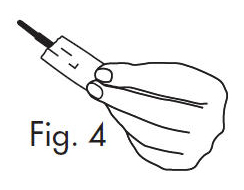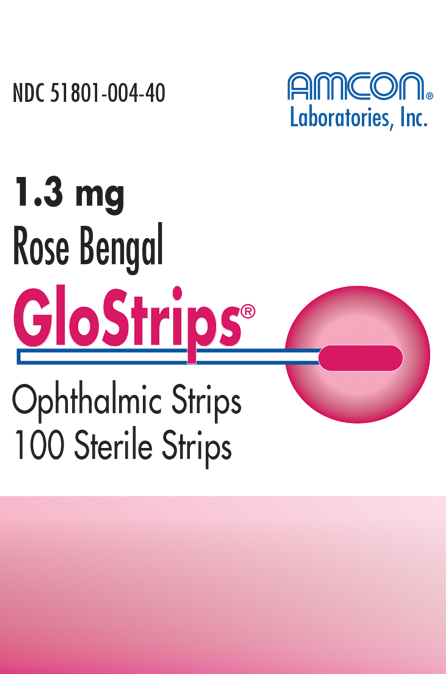 DRUG LABEL: GloStrips
NDC: 51801-004 | Form: STRIP
Manufacturer: Nomax Inc.
Category: prescription | Type: HUMAN PRESCRIPTION DRUG LABEL
Date: 20191223

ACTIVE INGREDIENTS: Rose Bengal Sodium 1.3 mg/1 1

GloStrips®

DESCRIPTION

Rose Bengal Ophthalmic Strips

diagnostic agent is for professional use only

Each strip is impregnated with 1.3 mg of Rose Bengal.

ACTION

As a vital stain, Rose Bengal stains both the nuclei and cell walls of dead or degenerated epithelial cells of the cornea and conjunctiva. Rose Bengal will also stain the mucus of the precorneal tear film.

INDICATIONS

Rose Bengal ophthalmic strips are used as a diagnostic agent in routine ocular examinations or when superficial conjunctiva or corneal tissue change is suspected. Rose Bengal ophthalmic strips can also serve as an effective aid in the diagnosis of keratoconjunctivitis sicca, keratitis, abrasions or corrosions as well as the detection of foreign bodies.

CONTRAINDICATIONS

Known hypersensitivity to Rose Bengal.

DIRECTIONS FOR USE

To ensure optimal staining and patient comfort, the GloStrip impregnated tip should be moistened with one or two drops of sterile, isotonic saline or irrigating solution before application. Shake off excess solution and touch conjunctiva or fornix as required with moistened tip. It is recommended that the patient blink several times after application.

NOTE

The contents may not be sterile if the individual strip package has been damaged or previously opened. This product is intended for external use only. Keep out of reach of children. Store below 30°C.

CAUTION

Take care not to stain clothing.

HOW SUPPLIED

Dispenser carton containing 100 sterile strips.

INSTRUCTIONS FOR OPENING STERILE GLOSTRIPS®

1.Grasp free tab ends of wrapping and slowly pull apart. When the white paper handle becomes visible, remove the GloStrip® from the envelope.

Fig. 1

An Alternate Method of Opening:

1.Grasp envelope firmly with two hands as shown in Fig. 2 below. Tear the envelope from both its edges to the strip handle.

Fig. 2

2.Hold the handle end of the GloStrip® with the left hand and the paper envelope without holding the tip with the right hand. See Fig. 3

Fig. 3

3.Separate the envelope at the tear, exposing the GloStrip® tip. See Fig. 4

Fig. 4

Nomax, Inc. • St. Louis, MO 63123 USA

Rev. 08/13
MSN 015-059

PRINCIPAL DISPLAY PANEL - 100 Strip Carton

NDC 51801-004-40

Amcon®
Laboratories, Inc.

Rose Bengal

GloStrips®

1.3 mg Rose Bengal
Ophthalmic Strips USP
100 Sterile Strips